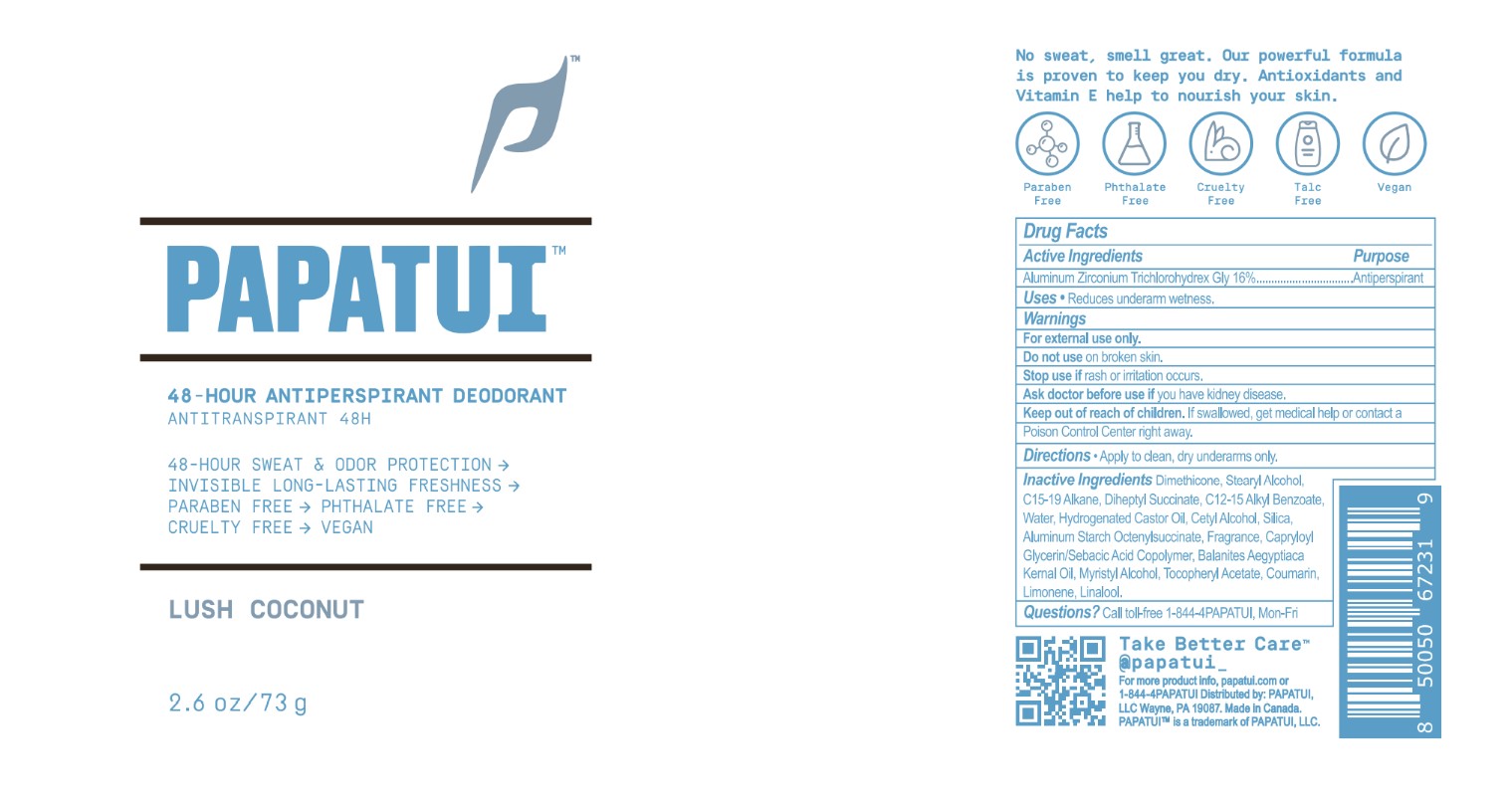 DRUG LABEL: Papatui Antiperspirant Deodorant Lush Coconut
NDC: 83850-102 | Form: STICK
Manufacturer: PAPATUI LLC
Category: otc | Type: HUMAN OTC DRUG LABEL
Date: 20241211

ACTIVE INGREDIENTS: ALUMINUM ZIRCONIUM TRICHLOROHYDREX GLY 16 g/100 g
INACTIVE INGREDIENTS: LINALOOL, (+)-; STEARYL ALCOHOL; CETYL ALCOHOL; DIMETHICONE; .ALPHA.-TOCOPHEROL ACETATE; LIMONENE, (+)-; C15-19 ALKANE; BALANITES AEGYPTIACA SEED OIL; COUMARIN; ALUMINUM STARCH OCTENYLSUCCINATE; CAPRYLOYL GLYCERIN/SEBACIC ACID COPOLYMER (2000 MPA.S); DIHEPTYL SUCCINATE; SILICON DIOXIDE; MYRISTYL ALCOHOL; WATER; ALKYL (C12-15) BENZOATE; HYDROGENATED CASTOR OIL

Papatui Antiperspirant Deodorant Lush Coconut (NDC 83850-102)

DESCRIPTION

PAPATUI™

48-Hour Antiperspirant Deodorant

Antitranspirant 48H

48-HOUR SWEAT & ODOR PROTECTION ->

INVISIBLE LONG-LASTING FRESHNESS ->

PARABEN FREE -> PHTHALATE FREE ->

CRUELTY FREE -> VEGAN

LUSH COCONUT

2.6 oz/73 g

Drug Facts

Active Ingredients

Aluminum Zirconium Trichlorohydrex Gly 16%

Purpose

Antiperspirant

Uses

Reduces underarm wetness.

Warnings

For external use only

Do not use on broken skin.

Stop use if rash or irritation occurs.

Ask doctor before use if you have kidney disease.

DOSAGE AND ADMINISTRATION

For external use only

Keep out of reach of children. If swallowed, get medical help or contact a Poison Control Center right away.

Uses

Reduces underarm wetness.

Directions

Apply to clean, dry underarms only.

Inactive Ingredients:

Dimethicone, Stearyl Alcohol, C15-19 Alkane, Diheptyl Succinate, C12-15 Alkyl Benzoate, Water, Hydrogenated Castor Oil, Cetyl Alcohol, Silica, Aluminum Starch Octenylsuccinate, Fragrance, Capryloyl Glycerin/Sebacic Acid Copolymer, Balanites Aegyptiaca Kernal Oil, Myristyl Alcohol, Tocopheryl Acetate, Coumarin, Limonene, Linalool.

Questions?

Call toll-free 1-844-4PAPATUI, Mon-Fri